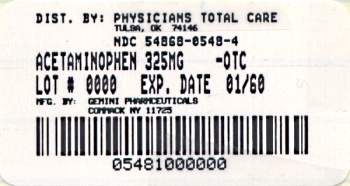 DRUG LABEL: Acetaminophen
NDC: 54868-0548 | Form: TABLET
Manufacturer: Physicians Total Care, Inc.
Category: otc | Type: HUMAN OTC DRUG LABEL
Date: 20091216

ACTIVE INGREDIENTS: ACETAMINOPHEN 325 mg/1 1
INACTIVE INGREDIENTS: POVIDONE; STARCH, CORN; SODIUM STARCH GLYCOLATE TYPE A POTATO; STEARIC ACID

Acetaminophen Tablets

*Compared to the active ingredient in Tylenol®

Drug Facts

ACTIVE INGREDIENT

(in each tablet)

Acetaminophen 325 mg

PURPOSES

Pain Reliever/Fever Reducer

USES

for the temporary relief of minor aches and pains due to:

- Headache
- Muscular aches
- Backache
- Minor pain of arthritis
- The common cold
- Toothache
- Premenstrual and menstrual cramps

Temporarily reduces fever.

WARNINGS

Liver warning:

This product contains acetaminophen. Severe liver damage may occur if

- adult takes more than 12 tablets in 24 hours, which is the maximum daily amount
- child takes more than 5 doses in 24 hours
- taken with other drugs containing acetaminophen
- adult has 3 or more alcoholic drinks every day while using this product

Do not use

- with any other drug containing acetaminophen (prescription or nonprescription). If you are not sure whether a drug contains acetaminophen, ask a doctor or pharmacist.
- if you are allergic to acetaminophen or any of the inactive ingredients in this product

Ask a doctor before use if the user has liver disease.

Ask a doctor or pharmacist before use if the user is taking the blood thinning drug warfarin.

Stop use and ask a doctor if

- Pain gets worse or lasts more than 10 days in adults and children
- Pain gets worse or lasts more than 5 days in children under 12 years
- Fever gets worse or lasts more than 3 days
- New symptoms occur
- Redness or swelling is present

These could be signs of a serious condition.

If pregnant or breast-feeding, ask a health professional before use.

Keep out of reach of children.

Keep out of reach of children.

OVERDOSAGE

Overdose warning:

Taking more than the recommended dose (overdose) may cause liver damage. In case of overdose, get medical help or contact a Poison Control Center right away. (1-800-222-1222). Quick medical attention is critical for adults as well as for children even if you do not notice any signs or symptoms.

DIRECTIONS

Do not take more than directed

Age | Dose
Adults and Children 12 years and over | - Take 2 tablets every 4 to 6 hours while symptoms last - Do not take more than 12 tablets in 24 hours
Children 6-11 years | - Take 1 tablet every 4 to 6 hours while symptoms last - Do not take more than 5 tablets in 24 hours
Children under 6 years | Do not use adult Regular Strength products in children under 6 years of age; this will provide more than the recommended dose (overdose) of acetaminophen and may cause liver damage.

OTHER INFORMATION

- Store at room temperature 15°-30°C (59°-86°F)
- Use by expiration date on package.

INACTIVE INGREDIETNS

Povidone, Pregelatinized Starch, Sodium Starch Glycolate, Stearic Acid

Questions? To report a Serious Adverse Event contact 1-877-835-5472.

*This product is not manufactured or distributed by McNeil Consumer Products Co., owners of the registered trademark Tylenol®.

Distributed by:

Amneal Pharmaceuticals

104 Hippocrates Way,

Glasgow, KY 42141

Rev. 11/2009

Relabeling of "Additional Barcode Label" by:
Physicians Total Care, Inc.
Tulsa, OK 74146

PACKAGE LABEL.PRINCIPAL DISPLAY PANEL

Acetaminophen Tablets

325 mg

Bottles of 50 | NDC 54868-0548-2
Bottles of 100 | NDC 54868-0548-4
Bottles of 1000 | NDC 54868-0548-3